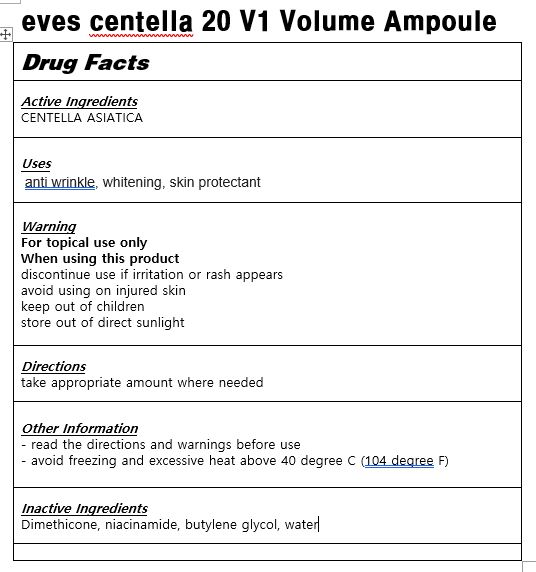 DRUG LABEL: eves volume V2 essence
NDC: 83113-0002 | Form: LIQUID
Manufacturer: eveskorea
Category: otc | Type: HUMAN OTC DRUG LABEL
Date: 20221121

ACTIVE INGREDIENTS: CENTELLA ASIATICA 1 g/100 mL
INACTIVE INGREDIENTS: WATER

Drug Facts

ACTIVE INGREDIENT

CENTELLA ASIATICA

PURPOSE

anti wrinkle, whitening

KEEP OUT OF REACH OF THE CHILDREN

INDICATIONS AND USAGE

take proper amount where needed

Keep out of reach of children.

Irritation around the eyes, ears, mucous membranes, including the mouth, under the skin irritation and rashes

Store in the room temperature

DOSAGE AND ADMINISTRATION

for oral use only

INACTIVE INGREDIENT

Dimethicone, niacinamide, butylene glycol, water